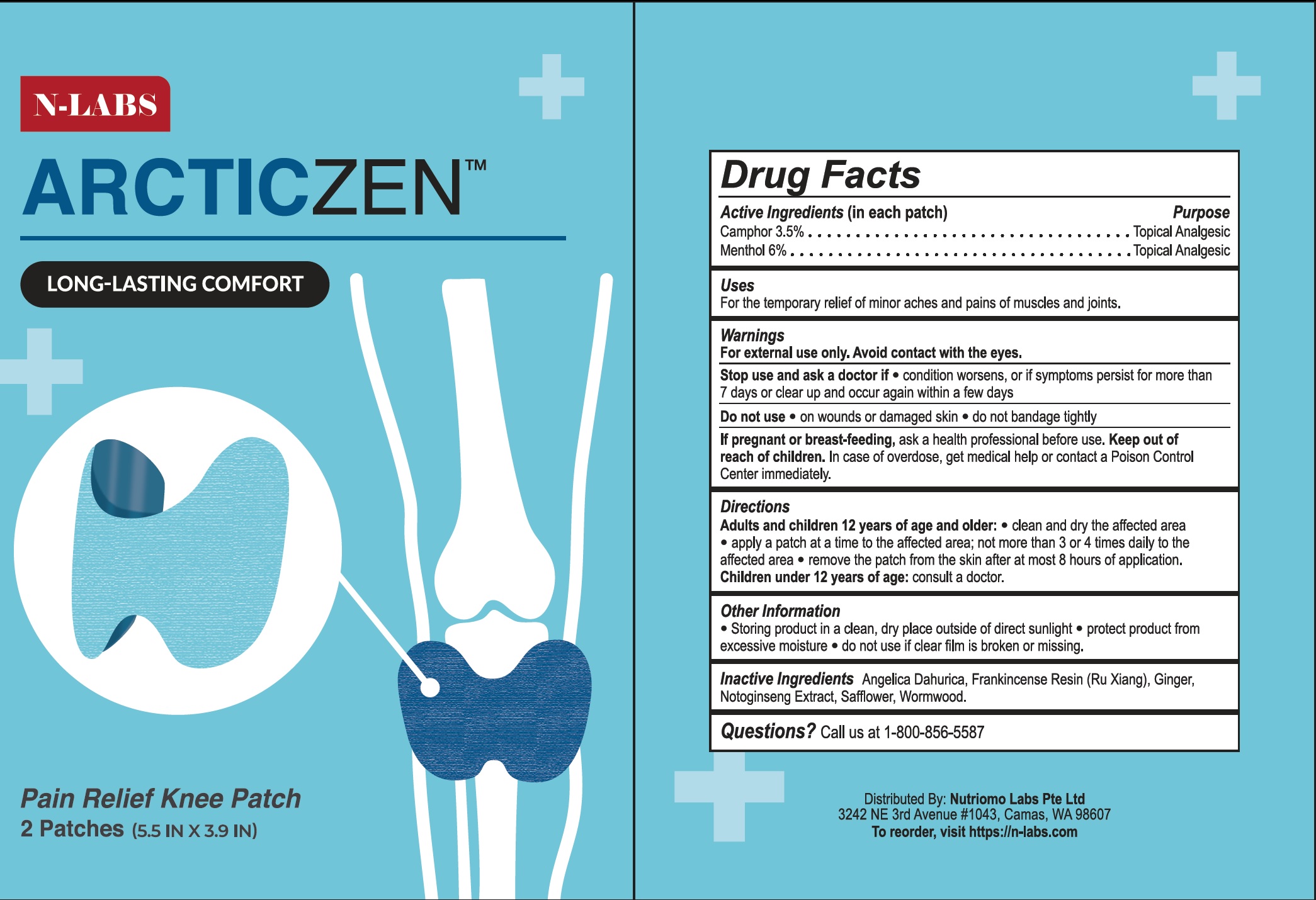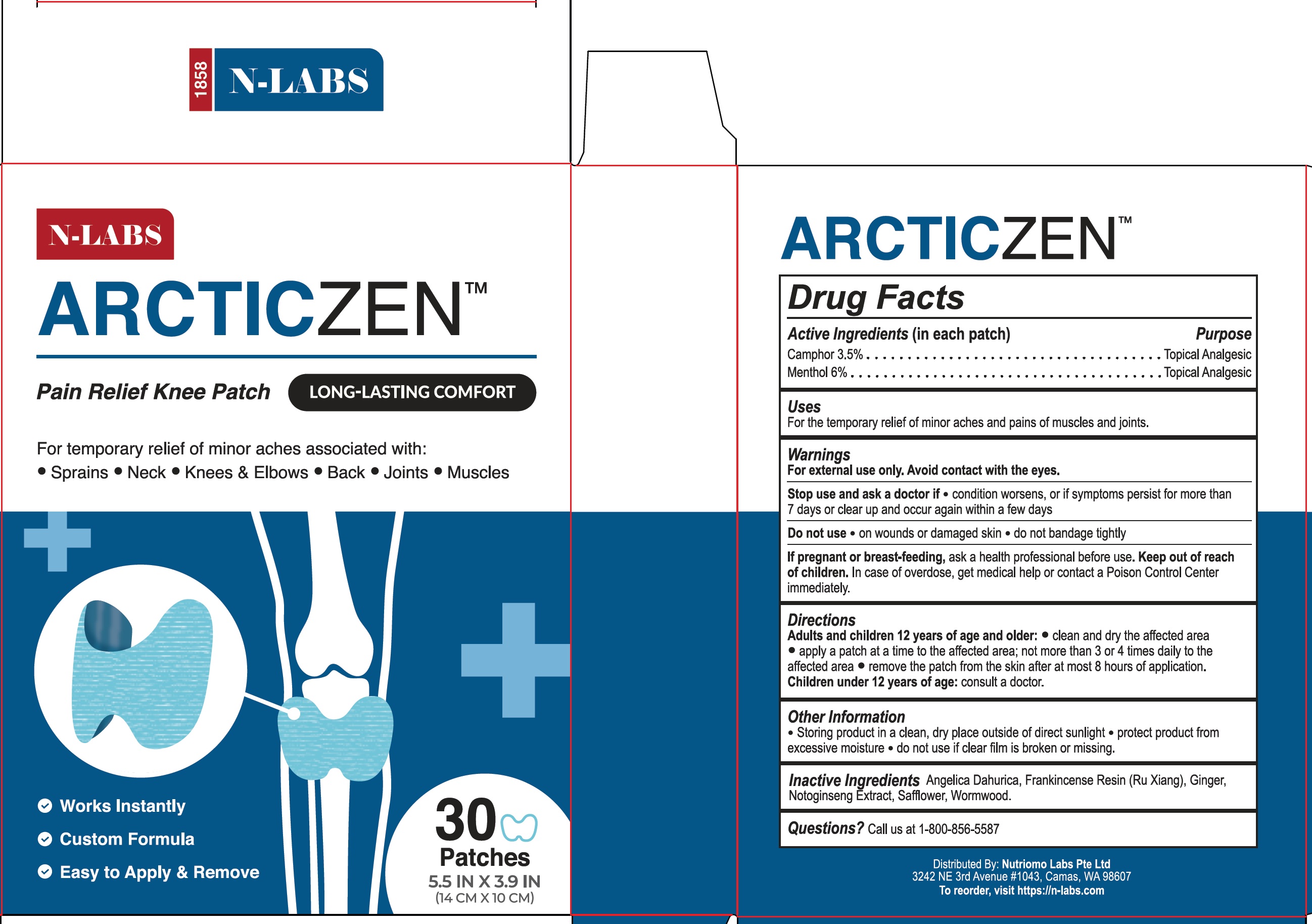 DRUG LABEL: N-Labs Arcticzen Pain Relief Knee
NDC: 71856-559 | Form: PATCH
Manufacturer: NUTRIOMO LABS PTE. LTD
Category: otc | Type: HUMAN OTC DRUG LABEL
Date: 20241226

ACTIVE INGREDIENTS: CAMPHOR (SYNTHETIC) 35 mg/1 g; MENTHOL 60 mg/1 g
INACTIVE INGREDIENTS: FRANKINCENSE; GINGER; SAFFLOWER; WORMWOOD

N-Labs Arcticzen Pain Relief Knee Patch

Active Ingredients(in each patch)

Camphor 3.5%
Menthol 6%

Purpose

Topical Analgesic

Uses

For the temporary relief of minor aches and pain of muscles and joints.

Warnings

For external use only. Avoid contact with the eyes.

Stop use and ask a doctor if

- condition worsens, or if symptoms persists for more than 7 days or clear up occur again within a few days

Do not use

- or wounds or damaged skin
- do not bandage tightly

If pregnant or breast-feeding,

ask a health professional before use.

Keep out of reach of children.

In case of overdose, get medical help or contact a Poison Control Center immediately.

Directions

Adults and children 12 years of age and older:

- clean and dry the affected area
- apply a patch at a time to the affected area; not more than 3 or 4 times daily to the affected area
- remove the patch from the skin after at most 8 hours of application.

Children under 12 years of age:consult a doctor.

Other Information

- Storing product in a clean, dry place outside of direct sunlight
- protect product from excessive moisture
- do not use if clear film is broken or missing.

Inactive Ingredients

Angelica Dahurica, Frankincense Resin (Ru Xiang), Ginger Notoginseng Extract, Safflower, Wormwood.

Questions?

Call us at 1-800-856-5587